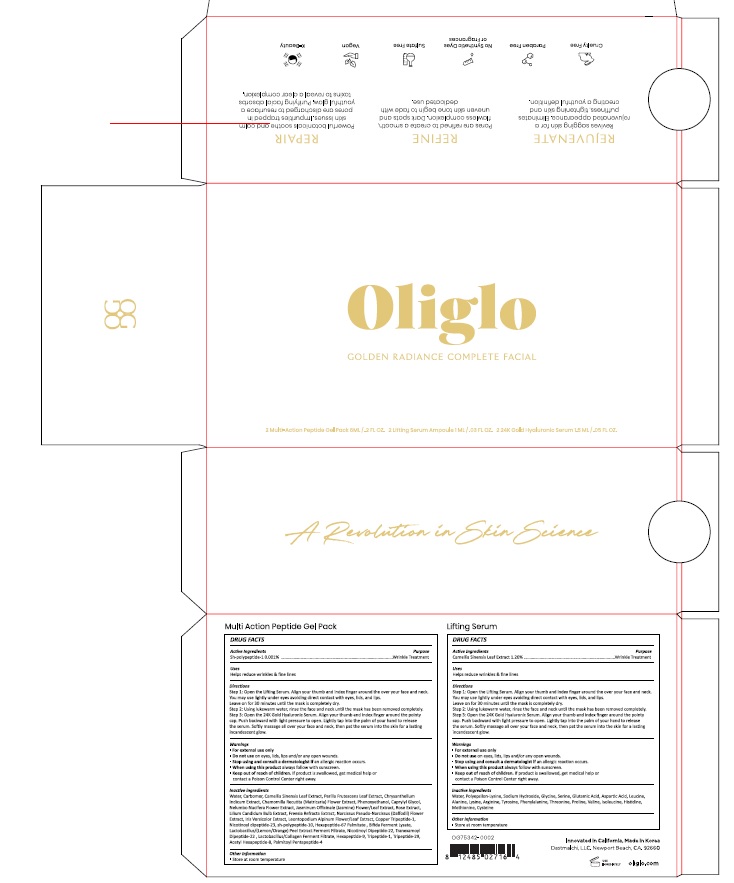 DRUG LABEL: Oliglo Golden Radiance Complete Facial
NDC: 73303-001 | Form: KIT | Route: TOPICAL
Manufacturer: Dastmalchi LLC
Category: otc | Type: HUMAN OTC DRUG LABEL
Date: 20191031

ACTIVE INGREDIENTS: BASIC FIBROBLAST GROWTH FACTOR (HUMAN) 0.001 g/100 mL; GREEN TEA LEAF 1.2 g/100 mL
INACTIVE INGREDIENTS: WATER; CARBOMER HOMOPOLYMER, UNSPECIFIED TYPE; GREEN TEA LEAF; PERILLA FRUTESCENS LEAF; CHRYSANTHELLUM INDICUM TOP; CHAMOMILE; PHENOXYETHANOL; CAPRYLYL GLYCOL; NELUMBO NUCIFERA FLOWER; JASMINUM OFFICINALE FLOWER; LILIUM CANDIDUM BULB; NARCISSUS PSEUDONARCISSUS FLOWER; LEONTOPODIUM NIVALE SUBSP. ALPINUM FLOWERING TOP; WATER; POLYEPSILON-LYSINE (4000 MW); SODIUM HYDROXIDE; GLYCINE; SERINE; GLUTAMIC ACID; ASPARTIC ACID; LEUCINE; ALANINE

73303-001_Oliglo Golden Radiance Complete Facial

ACTIVE INGREDIENT

sh-polypeptide-1, Camellia Sinensis Leaf Extract

INACTIVE INGREDIENT

Oliglo Lifting Serum

Water, Polyepsilon-Lysine, Sodium Hydroxide, Glycine, Serine, Glutamic Acid, Aspartic Acid, Leucine, Alanine, Lysine, Arginine, Tyrosine, Phenylalanine, Threonine, Proline , Valine, Isoleucine, Histidine, Methionine, Cysteine

Oliglo Multi-Action Peptide Gel Pack

Water, Carbomer, Camellia Sinensis Leaf Extract, Perilla Frutescens Leaf Extract, Chrysanthellum Indicum Extract, Chamomilla Recutita (Matricaria) Flower Extract, Phenoxyethanol, Caprylyl Glycol, Nelumbo Nucifera Flower Extract, Jasminum Officinale (Jasmine) Flower/Leaf Extract, Rose Extract, Lilium Candidum Bulb Extract, Freesia Refracta Extract, Narcissus Pseudo-Narcissus (Daffodil) Flower Extract, Iris Versicolor Extract, Leontopodium Alpinum Flower/Leaf Extract, Copper Tripeptide-1, Nicotinoyl dipeptide-23, sh-polypeptide-10, Hexapeptide-67 Palmitate , Bifida Ferment Lysate, Lactobacillus/(Lemon/Orange) Peel Extract Ferment Filtrate, Nicotinoyl Dipeptide-22, Tranexamoyl Dipeptide-22 , Lactobacillus/Collagen Ferment Filtrate, Hexapeptide-9, Tripeptide-1, Tripeptide-29, Acetyl Hexapeptide-8, Palmitoyl Pentapeptide-4

PURPOSE

Helps reduce wrinkles & fine lines

Keep out of reach of the children

INDICATIONS AND USAGE

Step 1: Open the Lifting Serum. Align your thumb and index finger around the over your face and neck. You may use lightly under eyes avoding direct contact with eyes, lids, and lips. Leave on for 30 minutes until the mask is completely dry.

Step 2: Using lukewarm water, rinse the face and neck until the mask has been removed completely.

Setp 3: Open the 24K Gold Hyaluronic Serum. Align your thumb and index finger around the pointy cap. Push backward with light pressure to open. Lightly tap into the palm of your hand to release the serum. Softly massage all over your face and neck, then pat the serum into the skin for a lasting incandescent glow.

WARNINGS

For External Use Only.

Do not use on eyes, lids, lips and/or any open wounds.

Steop using and consult a dermatologist if an allergic reaction occurs.

When using this product always follow with sunscreen.

Keep out of reach of children. If product is swallowed, get medical help or contact a Poison Control Center right away.

DOSAGE AND ADMINISTRATION

for external use only